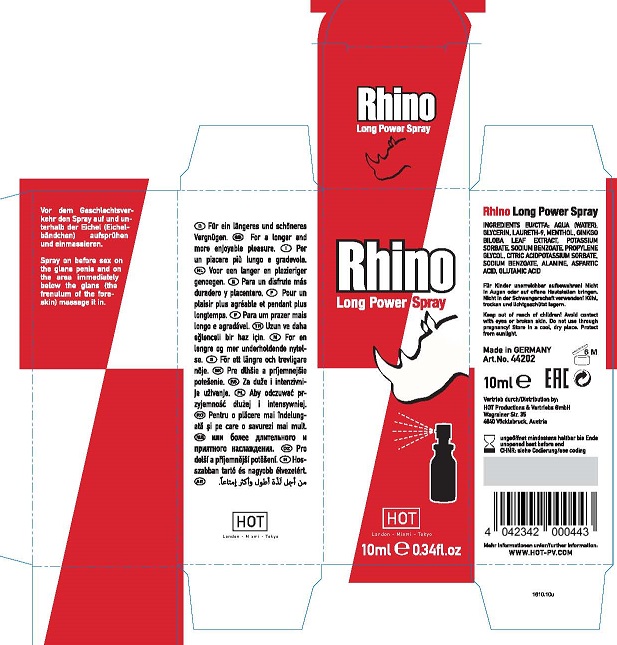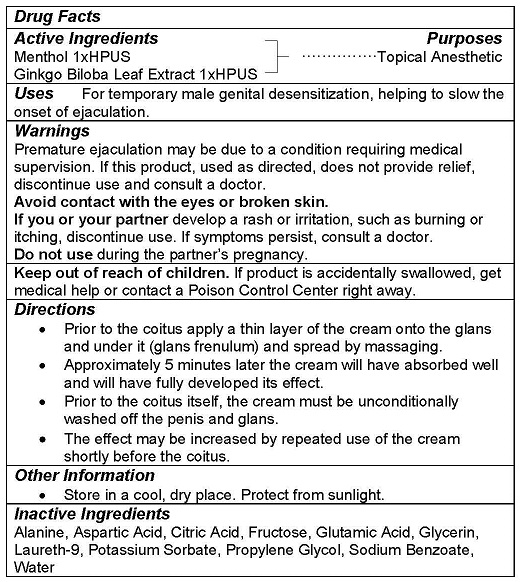 DRUG LABEL: RHINO LONG POWER
NDC: 71326-201 | Form: SPRAY
Manufacturer: HOT PRODUCTIONS AND VERTRIEBS GMBH
Category: homeopathic | Type: HUMAN OTC DRUG LABEL
Date: 20231005

ACTIVE INGREDIENTS: MENTHOL 1 g/100 mL; GINKGO 1 g/100 mL
INACTIVE INGREDIENTS: ALANINE; ASPARTIC ACID; ANHYDROUS CITRIC ACID; FRUCTOSE; GLUTAMIC ACID; GLYCERIN; POLIDOCANOL; POTASSIUM SORBATE; PROPYLENE GLYCOL; SODIUM BENZOATE; WATER

HOT PRODUCTS - Rhino Long Power Spray - 71326-201

ACTIVE INGREDIENTS

Menthol 1xHPUS
Ginkgo Biloba Leaf Extract 1xHPUS

PURPOSE

Topical Anesthetic

USE

For temporary male genital desensitization, helping to slow the onset of ejaculation.

WARNINGS

Premature ejaculation may be due to a condition requiring medical supervision. If this product, used as directed, does not provide relief, discontinue use and consult a doctor.
Avoid contact with the eyes or broken skin.
If you or your partner develop a rash or irritation, such as burning or itching, discontinue use. If symptoms persist, consult a doctor.
Do not use during the partner’s pregnancy.

Keep out of reach of children. If product is accidentally swallowed, get medical help or contact a Poison Control Center right away.

DIRECTIONS

- Prior to the coitus apply a thin layer of the cream onto the glans and under it (glans frenulum) and spread by massaging.
- Approximately 5 minutes later the cream will have absorbed well and will have fully developed its effect.
- Prior to the coitus itself, the cream must be unconditionally washed off the penis and glans.
- The effect may be increased by repeated use of the cream shortly before the coitus.

OTHER INFORMATION

- Store in a cool, dry place. Protect from sunlight.

INACTIVE INGREDIENTS

Alanine, Aspartic Acid, Citric Acid, Fructose, Glutamic Acid, Glycerin, Laureth-9, Potassium Sorbate, Propylene Glycol, Sodium Benzoate, Water